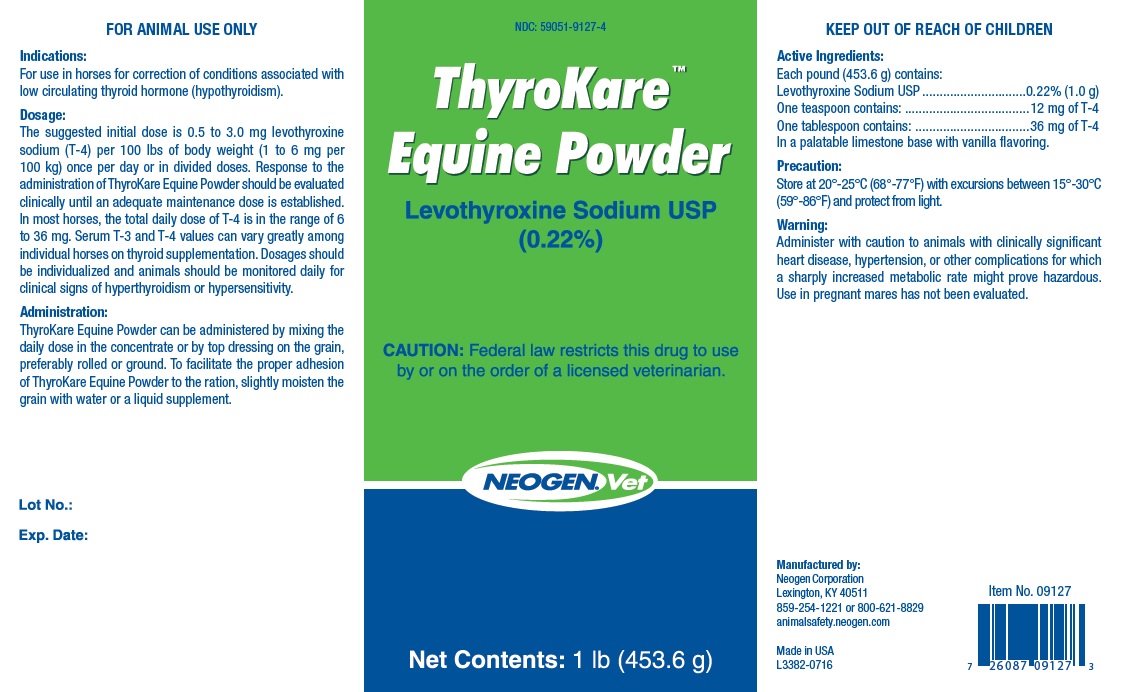 DRUG LABEL: ThyroKare
NDC: 59051-9127 | Form: Powder
Manufacturer: Neogen Corporation-Mercer Rd
Category: animal | Type: PRESCRIPTION ANIMAL DRUG LABEL
Date: 20181101

ACTIVE INGREDIENTS: LEVOTHYROXINE SODIUM 1 g/453.6 g

THYROKARE EQUINE POWDER

Indications:

For use in horses for correction of conditions associated with low circulating thyroid hormone (hypothyroidism).

Dosage:

The suggested initial dose is 0.5 to 3.0 mg levothyroxine sodium (T-4) per 100 lbs of body weight (1 to 6 mg per 100 kg) once per day or in divided doses. Response to the administration of ThyroKare Powder should be evaluated clinically until an adequate maintenance dose is established. In most horses, the total daily dose of T-4 is in the range of 6 to 36 mg. Serum T-3 and T-4 values can vary greatly among inidividual horses on thyroid supplementation. Dosages should be individualized and animals should be monitored daily for clinical signs of hyperthyroidism or hypersensitivity.

Administration:

ThyroKare Powder can be administered by mixing the daily dose in the concentrate or by top dressing on the grain, preferably rolled or ground. To facilitate the proper adhesion of ThyroKare Powder to the ration, slightly moisten the grain with water or a liquid supplement.

Precaution:

Store at 20°-25°C (68°-77°F) with excursions between 15°-30°C (59°-86°F) and protect from light.

Warning:

Administer with caution to animals with clinically significant heart disease, hypertension, or other complications for which a sharply increased metabolic rate might prove hazardous. Use in pregnant mares has not been evaluated.

Lot No.:

Exp. Date:

Manufactured by:

Neogen Corporation

Lexington, KY 40511

859-254-1221 or 800-621-8829

Made in USA

PRINCIPAL DISPLAY PANEL - 1 pound bottle

NDC: 59051-9127-4

ThyroKare Powder™

Levothyroxine Sodium USP

(0.22%)

CAUTION: Federal law restricts this drug to use by or on the order of a licensed veterinarian.

NEOGEN.Vet

Net Contents: 1 lb (453.6 g)

L3382-0716